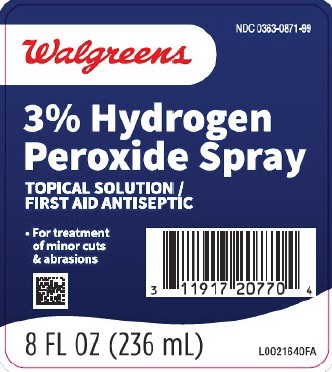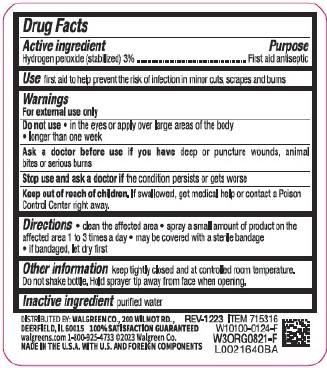 DRUG LABEL: Hydrogen Peroxide
NDC: 0363-0871 | Form: SOLUTION
Manufacturer: Walgreen Co.
Category: otc | Type: HUMAN OTC DRUG LABEL
Date: 20260212

ACTIVE INGREDIENTS: HYDROGEN PEROXIDE 30 mg/1 mL
INACTIVE INGREDIENTS: WATER

Walgreens 871.001/871AA
Hydrogen Peroxide

Active ingredient

Hydrogen peroxide (stabilized) 3%

Purpose

First Aid Antiseptic

Use

- first aid to help prevent the risk of infection in minor cuts, scrapes and burns

Warnings

For external use only

Do not use

- in the eyes or apply over large areas of the body
- longer than 1 week

Ask a doctor before use if you have

deep or puncture wounds, animal bites or serious burns

Stop use and ask a doctor if

- if condition persists or gets worse

Keep out of reach of children.

If swallowed, get medical help or contact a Poison Control Center right away.

Directions

- clean the affected area
- apply a small amount of product on the affected area 1 to 3 times a day
- may be covered with a sterile bandage
- if bandaged, let dry first

Other information

keep tightly closed and at controlled room temperature. Do not shake bottle. Hold away from face when opening.

inactive ingredient

purified water

ADVERSE REACTION

DISTRIBUTED BY: WALGREEN CO., 200 WILMOT RD.,

DEERFIELD, IL 60015 100% SATISFACTION GUARANTEED

walgreens.com 1-800-925-4733 ©2023 Walgreen Co.

MADE IN U.S.A. WITH U.S. AND FOREIGN COMPONENTS

Principal display panel

NDC 0363-0871-99

Walgreens

3% Hydrogen Peroxide Spray

Topical Solution / First Aid antiseptic

- For treatment of minor cuts & abrasions

8 FL OZ (236 mL)